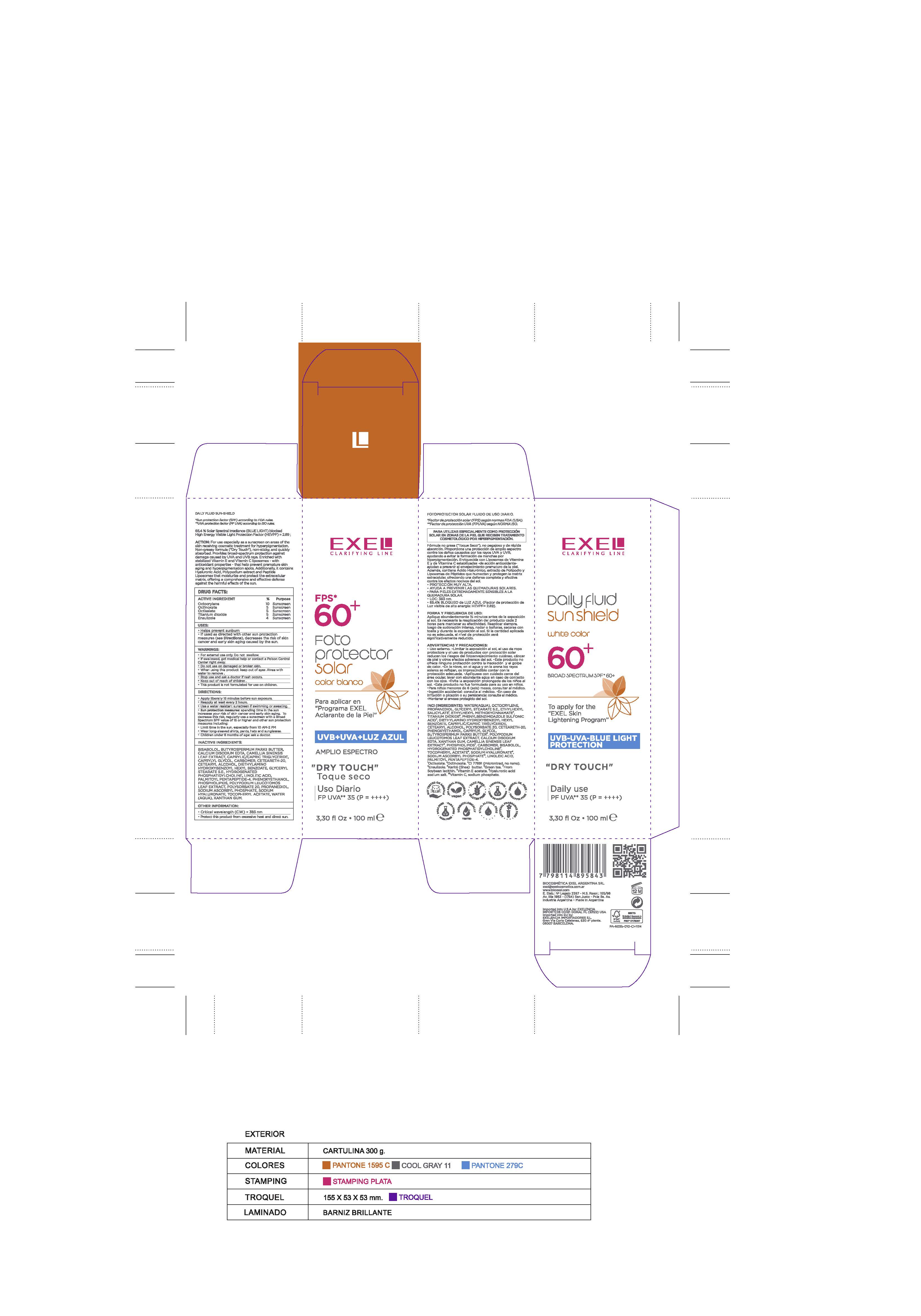 DRUG LABEL: EXEL CLARIFYING LINE DAILY FLUID SUN SHIELD WHITE COLOR BROAD SPECTRUM SPF 60 PLUS
NDC: 67623-004 | Form: CREAM
Manufacturer: Biocosmetica Exel Argentina SRL
Category: otc | Type: HUMAN OTC DRUG LABEL
Date: 20250101

ACTIVE INGREDIENTS: ENSULIZOLE 4 g/100 mL; OCTINOXATE 5 g/100 mL; OCTOCRYLENE 10 g/100 mL; TITANIUM DIOXIDE 5 g/100 mL; OCTISALATE 5 g/100 mL
INACTIVE INGREDIENTS: LINOLEIC ACID; WATER; BISABOLOL; DIETHYLAMINO HYDROXYBENZOYL HEXYL BENZOATE; LECITHIN, SOYBEAN; PHLEBODIUM AUREUM LEAF; PHENOXYETHANOL; PALMITOYL PENTAPEPTIDE-4; CAMELLIA SINENSIS LEAF; PROPANEDIOL; SODIUM HYALURONATE; CARBOMER INTERPOLYMER TYPE A (55000 CPS); BUTYROSPERMUM PARKII (SHEA) BUTTER; CAPRYLYL GLYCOL; SODIUM ASCORBYL PHOSPHATE; CALCIUM DISODIUM EDTA; CAPRYLIC/CAPRIC TRIGLYCERIDE; CETEARETH-20; CETEARYL ALCOHOL; HYDROGENATED SOYBEAN PHOSPHATIDYLCHOLINE; POLYSORBATE 20; XANTHAN GUM; GLYCERYL STEARATE SE; ALPHA-TOCOPHEROL ACETATE

Active ingredients , purpose

Octocrylene 10%, sunscreen
Octinoxate 5%, sunscreen
Octisalate 5%, sunscreen
Titanium dioxide 5%, sunscreen
Ensulizole 4 %, sunscreen

Uses

Helps prevent sunburn.
If used as directed with other sun-protection measures (see Directions) decreases the risk of skin cancer and early skin aging caused by the sun.

Warnings

For external use only. Do not swallow.
If swallowed, get medical help or contact a Poison Control Center right away.
Do not use on damaged or broken skin.
When using this product: keep out of eyes. Rinse with water to remove .
Stop use and ask a doctor if rash occurs .
Keep out of reach of children .
This product is not formulated for use in children.

Directions

Apply liberally 15 minutes before sun exposure.
Reapply at least every 2 hours.
Use a water resistant sunscreen if swimming or sweating.
Sun protection measures: spending time in the sun increases your risk of skin cancer and early skin aging. To decrease this risk, regularly use a sunscreen with a Broad Spectrum SPF value of 15 or higher and other sun protection measures including:
Limit time in the sun, especially from 10 AM-2 PM
Wear long-sleeved shirts, pants, hats and sunglasses.
Children under 6 months of age: ask a doctor.

Inactive Ingredients

BISABOLOL, BUTYROSPERMUM PARKII BUTTER, CALCIUM DISODIUM EDTA, CAMELLIA SINENSIS LEAF EXTRACT, CAPRYLIC/CAPRIC TRIGLYCERIDE, CAPRYLYL GLYCOL, CARBOMER, CETEARETH-20, CETEARYL ALCOHOL, DIETHYLAMINO HYDROXYBENZOYL HEXYL BENZOATE, GLYCERYL STEARATE S.E., HYDROGENATED PHOSPHATIDYLCHOLINE, LINOLEIC ACID, PALMITOYL PENTAPEPTIDE-4, PHENOXYETHANOL, PHOSPHOLIPIDS, POLYPODIUM LEUCOTOMOS LEAF EXTRACT, POLYSORBATE 20, PROPANEDIOL, SODIUM ASCORBYL PHOSPHATE, SODIUM HYALURONATE, TOCOPHERYL ACETATE, WATER (AQUA), XANTHAN GUM

Keep out of reach of children

DOSAGE AND ADMINISTRATION

.

INDICATIONS AND USAGE

.